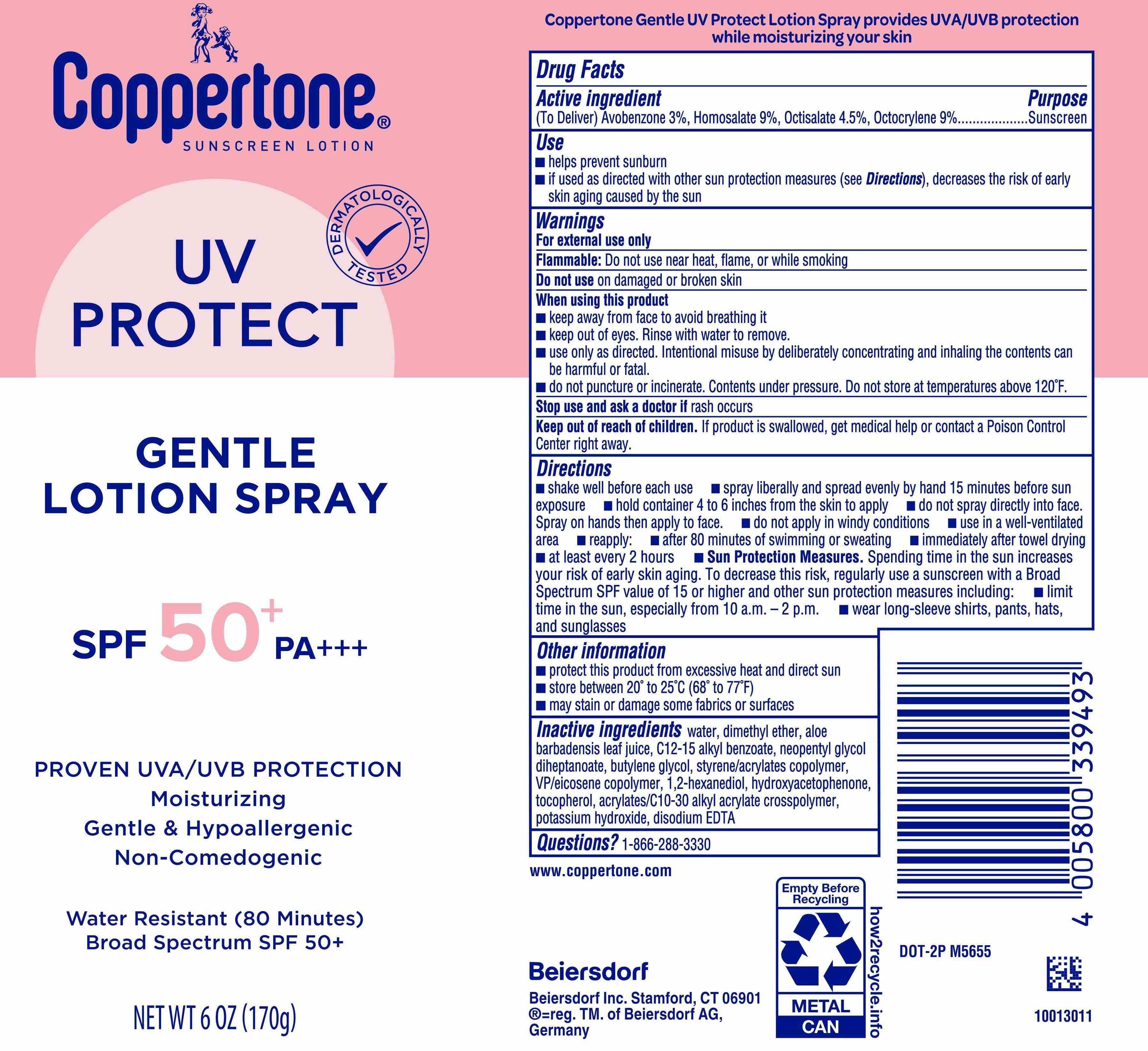 DRUG LABEL: Coppertone UV Protect Sunscreen SPF 50
NDC: 66800-0132 | Form: AEROSOL, SPRAY
Manufacturer: Beiersdorf Inc
Category: otc | Type: HUMAN OTC DRUG LABEL
Date: 20251231

ACTIVE INGREDIENTS: AVOBENZONE 3 g/100 g; HOMOSALATE 9 g/100 g; OCTOCRYLENE 9 g/100 g; OCTISALATE 4.5 g/100 g
INACTIVE INGREDIENTS: DIMETHYL ETHER; ALKYL (C12-15) BENZOATE; ALOE VERA LEAF; TOCOPHEROL; ACRYLATES/C10-30 ALKYL ACRYLATE CROSSPOLYMER (60000 MPA.S); POTASSIUM HYDROXIDE; WATER; STYRENE/ACRYLAMIDE COPOLYMER (MW 500000); 1,2-HEXANEDIOL; BUTYLENE GLYCOL; HYDROXYACETOPHENONE; NEOPENTYL GLYCOL DIHEPTANOATE; VINYLPYRROLIDONE/EICOSENE COPOLYMER; DISODIUM EDTA-COPPER

Coppertone UV Protect Lotion Spray Sunscreen SPF 50

Active ingredients

Avobenzone 3%, Homosalate 9%, Octisalate 4.5%, Octocrylene 9%

Purpose

Sunscreen

Uses

- helps prevent sunburn
- if used as directed with other sun protection measures (see Directions), decreases the risk of early skin aging caused by the sun

Warnings

- For external use only
- Flammable:Do not use near heat, flame, or while smoking

Do not useon damaged or broken skin

When using this product

- Keep away from face to avoid breathing it
- keep out of eyes. Rinse with water to remove.
- use only as directed. Intentional misuse by deliberately concentrating and inhaling the contents can be harmful or fatal.
- do not puncture or incinerate. Conents under pressure. Do not store at termperature above 120°F.

Stop use and ask a doctor ifrash occurs

Keep out of reach of children.If product is swallowed, get medical help or contact a Poison Control Center right away.

Directions

■ shake well before each use

■ spray liberally and spread evenly by hand 15 minutes before sun exposure

■ hold container 4 to 6 inches from the skin to apply

■ do not spray directly into face. Spray on hands then apply to face.

■ do not apply in windy conditions

■ use in a well-ventilated area

■ reapply:

■ after 80 minutes of swimming or sweating

■ immediately after towel drying

■ at least every 2 hours

■ Sun Protection Measures.Spending time in the sun increases your risk of skin cancer and early skin aging. To decrease this risk, regularly use a sunscreen with a Broad Spectrum SPF value of 15 or higher and other sun protection measures including:

■ limit time in the sun, especially from 10 a.m. – 2 p.m.

■ wear long-sleeve shirts, pants, hats, and sunglasses

■ children under 6 months: Ask a doctor

Other information

■ protect this product from excessive heat and direct sun

■ store between 20° to 25°C (68° to 77°F)

■ may stain or damage some fabrics or surfaces

Inactive ingredients

water, dimethyl ether, aloe barbadensis leaf juice, C12-15 alkyl benzoate, neopentyl glycol diheptanoate, butylene glycol, styrene/acrylates copolymer, VP/eicosene copolymer, 1,2-hexanediol, hydroxyacetophenone, tocopherol, acrylates/C10-30 alkyl acrylate crosspolymer, potassium hydroxide, disodium EDTA

Questions?

1-866-288-3330

PACKAGE LABEL

Coppertone Sunscreen Lotion

UV Protect

Gentle Lotion Spray

SPF 50+ PA+++

Proven UVA/UVB Protection

Moisturizing

Gentle & Hypoallergenic

Non-Comedogenic

Water Resistan (80 Minutes)

Broad Specturm SPF 50+